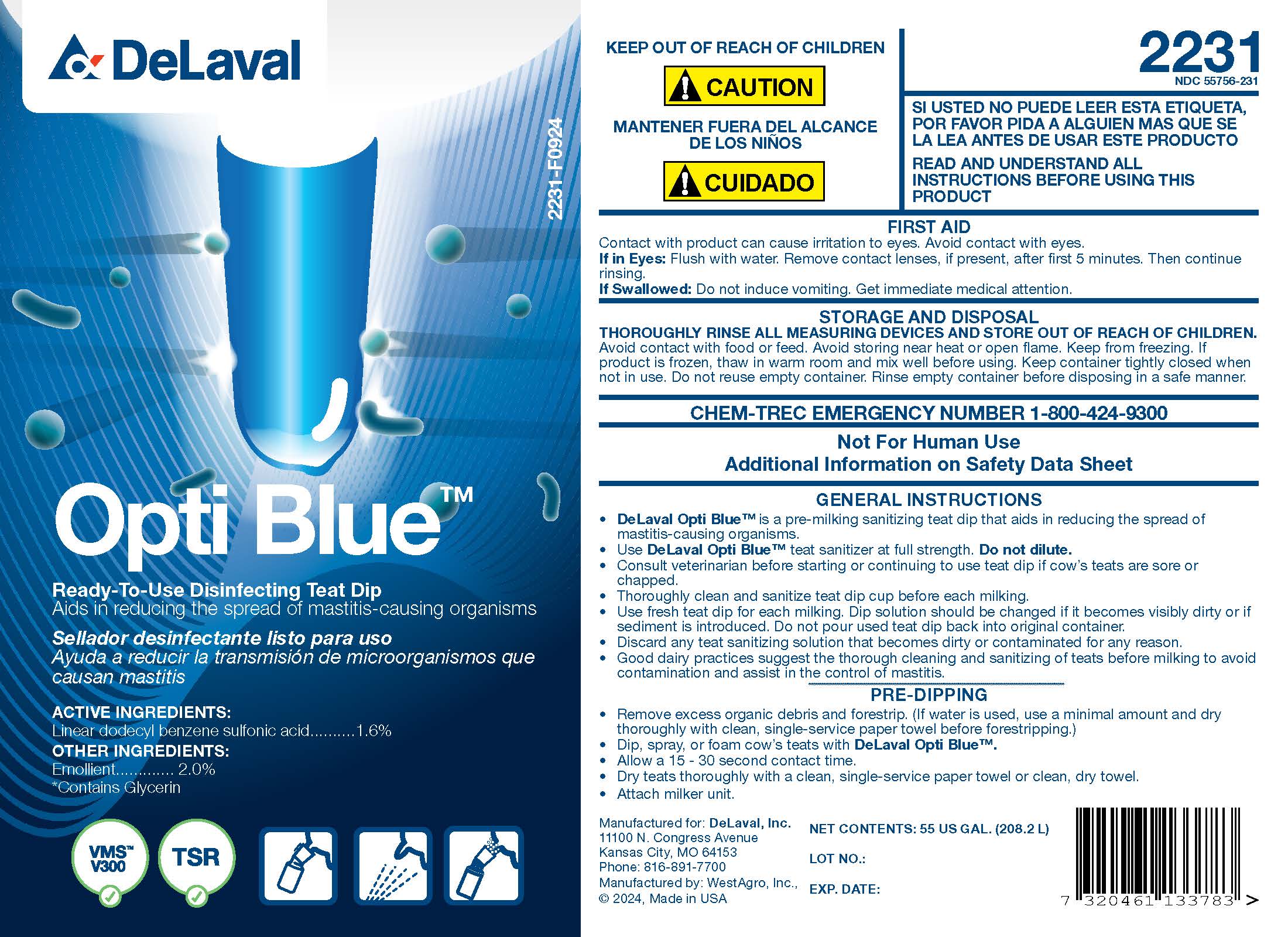 DRUG LABEL: Opti Blue
NDC: 55756-231 | Form: SOLUTION
Manufacturer: DeLaval
Category: animal | Type: OTC ANIMAL DRUG LABEL
Date: 20241219

ACTIVE INGREDIENTS: DODECYLBENZENESULFONIC ACID 16.2 g/1 L

Opti Blue

INDICATIONS AND USAGE

Ready-To-Use Disinfecting Teat DipAids in reducing the spread of mastitis-causing organisms

ACTIVE INGREDIENTS:
Linear dodecyl benzene sulfonic acid ...................... 1.6%

INACTIVE INGREDIENT

OTHER INGREDIENTS:

Emollient* ............... 2.0%

*Contains Glycerin

KEEP OUT OF REACH OF CHILDREN

! CAUTION

MANTENER FUERA DEL ALCANCE DE LOS NINOS

! CUIDADO

2231
NDC 55756-231

SI USTED NO PUEDE LEER ESTA ETIQUETA, POR FAVOR PIDA A ALGUIEN MAS QUE SE LA LEA ANTES DE USAR ESTE PRODUCTO

READ AND UNDERSTAND ALL INSTRUCTIONS BEFORE USING THIS PRODUCT

FIRST AID
Contact with product can cause irritation to eyes. Avoid contact with eyes.
If in Eyes: Flush with water. Remove contact lenses, if present, after first 5 minutes. The continue rinsing.
If Swallowed: Do not induce vomiting. Get immediate medical attention.

STORAGE AND DISPOSAL
THOROUGHLY RINSE ALL MEASURING DEVICES AND STORE OUT OF REACH OF CHILDREN. Avoid contact with food or feed. Avoid storing near heat or open flame. Keep from freezing. If product is frozen, thaw in warm room and mix well before using. Keep container tightly closed when not in use. Do not reuse empty container. Rinse empty container before disposing in a safe manner.

CHEM-TREC EMERGENCY NUMBER 1-800-424-9300

Not for Human Use

Additional Information on Material Safety Data Sheet

GENERAL INSTRUCTIONS

- DeLaval Opti Blue™ is a pre-milking sanitizing teat dip that aids in reducing the spread of mastitis-causing organisms.
- Use DeLaval Opti Blue™ teat sanitizer at full strength. Do not dilute.
- Consult veterinarian before starting or continuing to use teat dip if cow's teats are sore or chapped.
- Thoroughly clean and sanitize teat dip cup before each milking.
- Use fresh teat dip for each milking. Dip solution should be changed if it becomes visibly dirty or if sediment is introduced. Do not pour used teat dip back into original container.
- Discard any teat sanitizing solution that becomes dirty or contaminated for any reason.
- Good dairy practices suggest the thorough cleaning and sanitizing of teats before milking to avoid contamination and assist in the control of mastitis.

PRE-DIPPING

- Remove excess organic debris and forestrip. (If water is used, use a minimal amount and dry thoroughly with clean, single-service paper towel before forestripping.)
- Dip, spray, or foam cow's teats with DeLaval Opti Blue.
- Allow a 15 - 30 second contact time.
- Dry teats thoroughly with a clean, single-service paper towel or clean, dry towel.
- Attach milker unit.

Manufactured for: DeLaval, Inc.
11100 N. Congress Avenue
Kansas City, MO 64153
Phone: 816-891-7700
Manufactured by: WestAgro, Inc.
©2024, Made in USA

NET CONTENTS:

LOT NO.:

EXP. DATE:

PACKAGE LABEL

Add image transcription here...